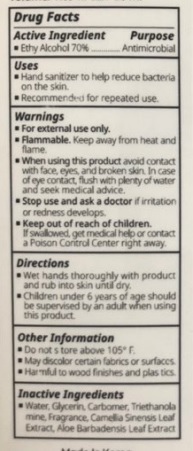 DRUG LABEL: CHOBS-READY TO HAND SANITIZER
NDC: 74122-0011 | Form: GEL
Manufacturer: CH Harmony Co., Ltd.
Category: otc | Type: HUMAN OTC DRUG LABEL
Date: 20200402

ACTIVE INGREDIENTS: ALCOHOL 35 mL/50 mL
INACTIVE INGREDIENTS: WATER

CH Harmony Co., Ltd. - CHOBS-READY TO HAND SANITIZER

ACTIVE INGREDIENT

Alcohol

INACTIVE INGREDIENT

water, glycerin, triethanolamine, etc

PURPOSE

Antiseptic

keep out of reach of the children

INDICATIONS AND USAGE

Place enough product in your palm to thoroughly spread on both hands and rub into the skin until dry.

Supervise children in the use of this product.

WARNINGS

For external use only.

Flammable.

Keep away from fire or flame.

DOSAGE AND ADMINISTRATION

for external use only